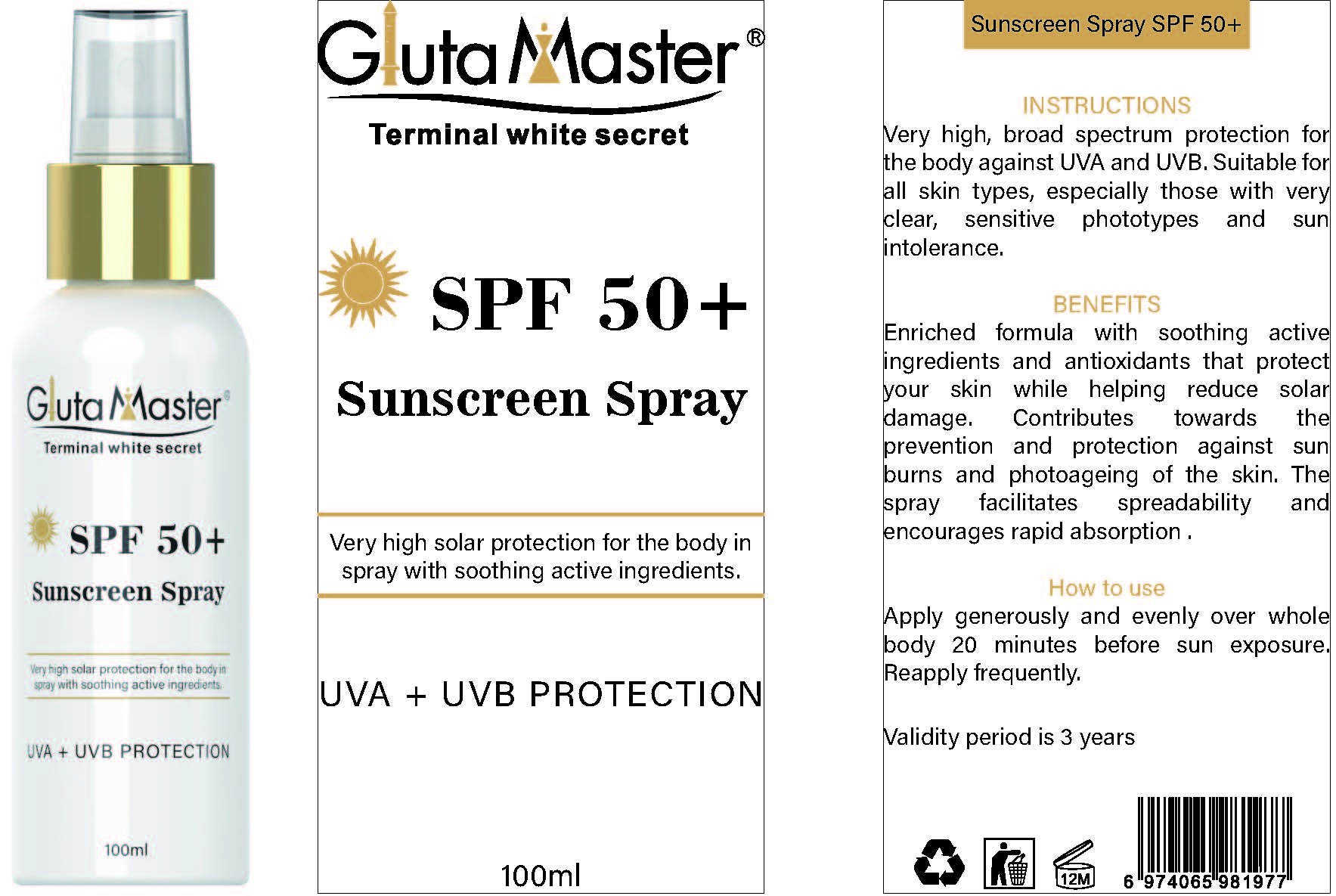 DRUG LABEL: SunscreenSpray
NDC: 84423-090 | Form: SPRAY
Manufacturer: Guangzhou Kadiya Biotechnology Co., Ltd.
Category: otc | Type: HUMAN OTC DRUG LABEL
Date: 20250803

ACTIVE INGREDIENTS: NIACINAMIDE 1 g/100 g; ZINC OXIDE 6 g/100 g
INACTIVE INGREDIENTS: CI 19140; GLYCERYL STEARATE; C13-16 ISOPARAFFIN; BUTYLENE GLYCOL; POTASSIUM CETYL PHOSPHATE; PROPYLPARABEN; CETEARETH-20; AQUA; METHYLPARABEN; 3-O-ETHYL ASCORBIC ACID; CETEARYL ALCOHOL; ALLANTOIN; EDETATE DISODIUM; MINERAL OIL; UREA; TROLAMINE; IODOPROPYNYL BUTYLCARBAMATE; CARBOMER; DMDM HYDANTOIN; PEG-100 STEARATE; GLYCERIN; DIMETHICONE

PURPOSE

Apply generously and evenly over wholebody 20 minutes before sun exposure.Reapply frequently

INACTIVE INGREDIENT

AQUA
MINERAL OIL
GLYCERIN
CETEARYL ALCOHOL
UREA
DIMETHICONE
GLYCERYL STEARATE
CETEARETH-20
POTASSIUM CETYL PHOSPHATE
PEG-100 STEARATE
TRIETHANOLAMINE
ALLANTOIN
CARBOMER
C13-16 ISOALKANE
DMDM HYDANTOIN
AROMA
METHYLPARABEN
PROPYLPARABEN
3-O-ETHYL ASCORBIC ACID
DISODIUM EDTA
BUTYLENE GLYCOL
IODOPROPYNYL BUTYLCARBAMATE
CI 19140

WARNINGS

1、For external use only, avoid contact with eyes when used
2、Keep out of reach of children

INDICATIONS AND USAGE

Very high, broad spectrum protection for the body against UVA and UVB. Suitable for all skin types, especially those with very clear, sensitive phototypes and sun intolerance.

DOSAGE AND ADMINISTRATION

Apply generously and evenly over whole body 20 minutes before sun exposure. Reapply frequently.

KEEP OUT OF REACH OF CHILDREN SECTION

Active Ingredients
NIACINAMIDE1mg/
Zinc oxide6%

PACKAGE LABEL

Active Ingredients
NIACINAMIDE1mg/
Zinc oxide6%

Uses：
Apply generously and evenly over wholebody 20 minutes before sun exposure.Reapply frequently.
The storage method：
Store sealed in a cool place and out of sunlight

AQUA
MINERAL OIL
GLYCERIN
CETEARYL ALCOHOL

UREA
DIMETHICONE
GLYCERYL STEARATE
CETEARETH-20
POTASSIUM CETYL PHOSPHATE
PEG-100 STEARATE
TRIETHANOLAMINE
ALLANTOIN
CARBOMER
C13-16 ISOALKANE
DMDM HYDANTOIN
AROMA
METHYLPARABEN
PROPYLPARABEN
3-O-ETHYL ASCORBIC ACID
DISODIUM EDTA
BUTYLENE GLYCOL
IODOPROPYNYL BUTYLCARBAMATE
CI 19140